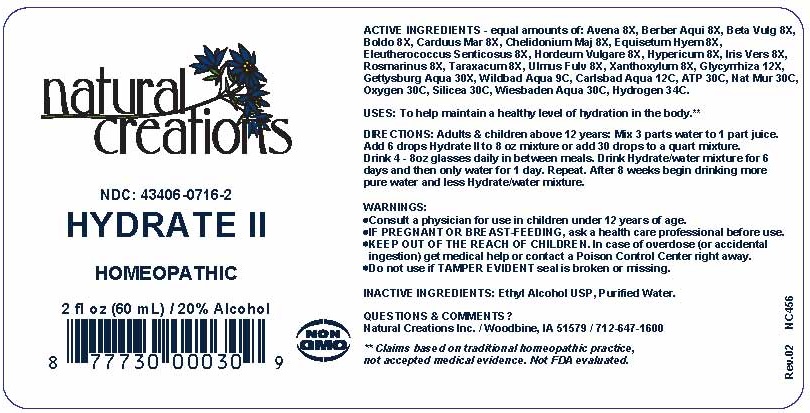 DRUG LABEL: Hydrate 2
NDC: 43406-0716 | Form: LIQUID
Manufacturer: Natural Creations, Inc
Category: homeopathic | Type: HUMAN OTC DRUG LABEL
Date: 20251216

ACTIVE INGREDIENTS: AVENA SATIVA FLOWERING TOP 8 [hp_X]/1 mL; BERBERIS AQUIFOLIUM ROOT BARK 8 [hp_X]/1 mL; BETA VULGARIS 8 [hp_X]/1 mL; PEUMUS BOLDUS LEAF 8 [hp_X]/1 mL; MILK THISTLE 8 [hp_X]/1 mL; CHELIDONIUM MAJUS 8 [hp_X]/1 mL; EQUISETUM HYEMALE 8 [hp_X]/1 mL; ELEUTHEROCOCCUS SENTICOSUS WHOLE 8 [hp_X]/1 mL; HORDEUM VULGARE WHOLE 8 [hp_X]/1 mL; HYPERICUM PERFORATUM 8 [hp_X]/1 mL; IRIS VERSICOLOR ROOT 8 [hp_X]/1 mL; ROSMARINUS OFFICINALIS FLOWERING TOP 8 [hp_X]/1 mL; TARAXACUM OFFICINALE 8 [hp_X]/1 mL; ULMUS RUBRA BARK 8 [hp_X]/1 mL; ZANTHOXYLUM AMERICANUM BARK 8 [hp_X]/1 mL; GLYCYRRHIZA GLABRA 12 [hp_X]/1 mL; ADENOSINE TRIPHOSPHATE 30 [hp_C]/1 mL; HYDROGEN 34 [hp_C]/1 mL; SODIUM CHLORIDE 30 [hp_C]/1 mL; OXYGEN 30 [hp_C]/1 mL; SILICON DIOXIDE 30 [hp_C]/1 mL
INACTIVE INGREDIENTS: ALCOHOL; WATER

HYDRATE II

ACTIVE INGREDIENT

ACTIVE INGREDIENTS: equal amounts of: Avera 8X, Berber Aui 8X, Beta Vulg 8X, Boldo 8X, Carduus Mar 8X, Chelidonium Maj 8X, Equisetum Hyem 8X, Eleutherococcus Senticosus 8X, Hordeum Vulgare 8X, Hypericum 8X, Iris Vers 8X, Rosmarinus 8X, Taraxacum 8X, Ulmus Fulv 8X, Xanthoxylum 8X, Gettysburg Aqua 12X, Glycyrrhiza 12X, Wildbad Aqua 9C, Carlsbad Aqua 12C, ATP 30C, Nat Mur 30C, Oxygen 30C, Silicea 30C, Wiesbaden Aqua 30C, Hydrogen 34C.

INDICATIONS AND USAGE

USES: To help maintain a healthy level of hydration in the body.**

PURPOSE

USES: To help maintain a healthy level of hydration in the body.**

DOSAGE AND ADMINISTRATION

DIRECTIONS: Adults & children above 12 years: Mix 3 parts water to 1 part juice. Add 6 drops Hydrate II to 8oz mixture or add 30 drops to a quart mixture. Drink 4 - 8 oz glasses daily between meals. Drink Hydrate/water mixture for 6 days and then only water for 1 day. Repeat. After 8 weeks begin drinking more pure water and less Hydrate/water mixture.

KEEP OUT OF REACH OF CHILDREN

KEEP OUT OF THE REACH OF CHILDREN. In case of overdose (or accidental ingestion) get medical help or contact a Poison Control Center right away.

WARNINGS:

- Consult a physician for use in children under 12 years of age.
- IF PREGNANT OR BREAST-FEEDING, ask a health care professional before use.
- KEEP OUT OF THE REACH OF CHILDREN. In case of overdose (or accidental ingestion) get medical help or contact a Poison Control Center right away.
- Do not use if TAMPER EVIDENT seal is broken or missing.

INACTIVE INGREDIENTS: Ethyl Alcohol USP, Purified Water.

QUESTIONS & COMMENTS?

Natural Creations, Inc. / Woodbine, IA 51579 / 712-647-1600

REFERENCES

**Claims based on traditional homeopathic practice, not accepted medical evidence. Not FDA evaluated.

PACKAGE LABEL

NDC: 43406-0716-2

HYDRATE II

HOMEOPATHIC

2 fl oz (60 mL) / 20% Alcohol